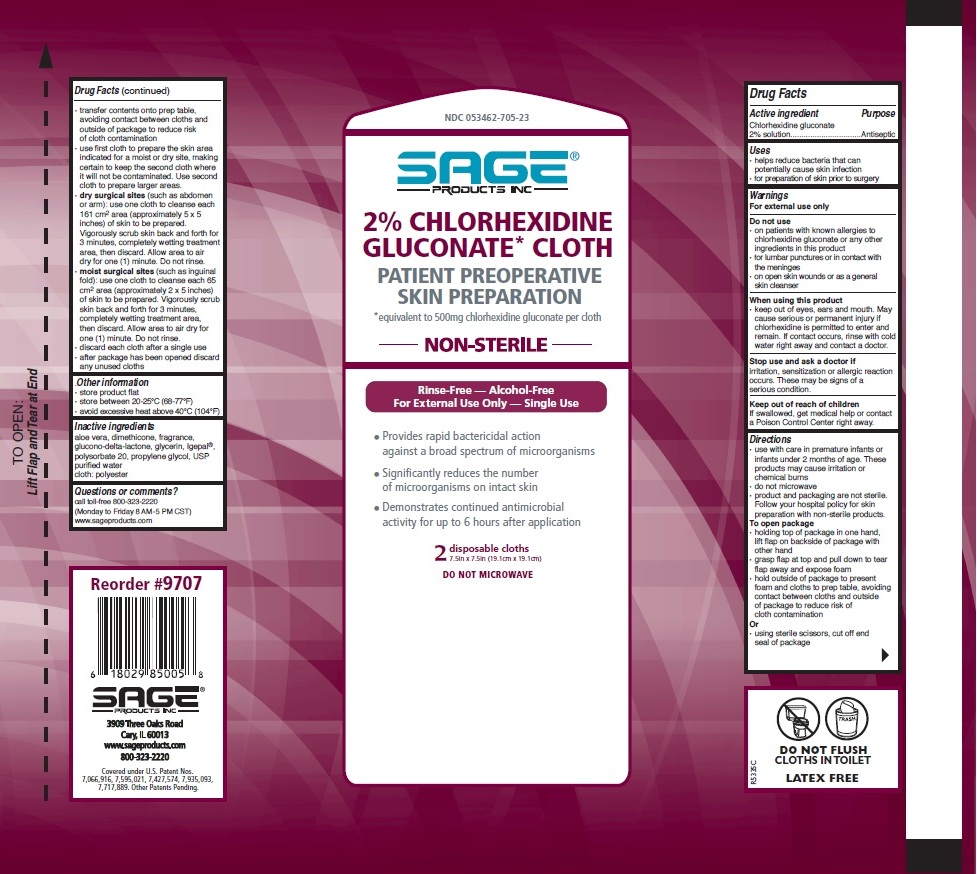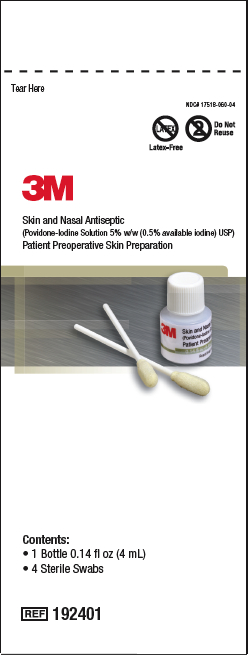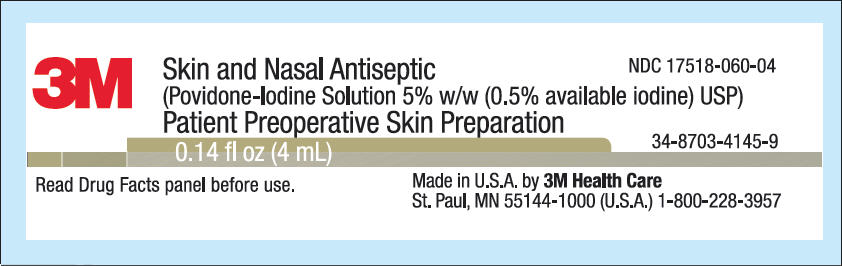 DRUG LABEL: Skin antisepsis, oral cleansing, nasal antisepsis
NDC: 53462-008 | Form: KIT | Route: TOPICAL
Manufacturer: Sage Products, Inc.
Category: otc | Type: HUMAN OTC DRUG LABEL
Date: 20121022

ACTIVE INGREDIENTS: chlorhexidine gluconate 500 mg/1 1; POVIDONE-IODINE 5 mg/1 mL
INACTIVE INGREDIENTS: water; nonoxynol-9; polysorbate 20; dimethicone 350; propylene glycol; aloe vera leaf; glycerin; gluconolactone; LACTIC ACID; LAURAMIDOPROPYLAMINE OXIDE; MALIC ACID; SODIUM HYDROXIDE; SODIUM IODIDE; PEG-100 STEARATE; WATER; XYLITOL

2% Chlorhexidine Gluconate Cloth and 3M Skin and Nasal Antiseptic

Active ingredient

chlorhexidine gluconate 2% solution

Povidone-Iodine USP, 5%

Purpose

Antiseptic

Keep out of reach of children.

If swallowed, get medical help or contact a Poison Control Center right away.

Uses

- helps reduce bacteria that can potentially cause skin infection
- for preparation of skin prior to surgery

Warnings

For external use only

Do not use

- on patients with known allergies to chlorhexidine gluconate or any other ingredients in this product
- for lumbar punctures or in contact with the meninges
- on open skin wounds or as a general skin cleanser

When using this product

- keep out of eyes, ears, and mouth. May cause serious or permanent injury if chlorhexidine is permitted to enter and remain. If contact occurs, rinse with cold water right away and contact a doctor.

Do not use if you have a known sensitivity to iodine or any other ingredient in this product. Do not use in eyes. If product gets into eyes, flush immediately with water. Do not use on infants less than 2 months old due to the risk of increased blood iodine levels.

Stop use and ask a doctor if irritation, sensitization or allergic reaction occurs. These may be signs of a serious condition.

Directions

2% Chlorhexidine Gluconate Cloth

- use with care in premature infants or infants under 2 months of age. These products may cause irritation or chemical burns.
- do not microwave
- product and packaging are not sterile. Follow your hospital policy for skin preparation with non-sterile products.

To open package

- holding top of package in one hand, lift flap on backside of package with other hand
- grasp flap at top and pull down to tear flap away and expose foam
- hold outside of package to present foam and cloths to prep table, avoiding contact between cloths and outside of package to reduce risk of cloth contamination.

Or

- using sterile scissors, cut off end seal of package
- transfer contents onto prep table, avoiding contact between cloths and outside of package to reduce risk of cloth contamination
- use first cloth to prepare the skin area indicated for a moist or dry site, making certain to keep the second cloth where it will not be contaminated. Use second cloth to prepare larger areas.
- dry surgical sites (such as abdomen or arm): use one cloth to cleanse each 161 cm2 area (approximately 5 x 5 inches) of skin to be prepared. Vigorously scrub skin back and forth for 3 minutes, completely wetting treatment area, then discard. Allow area to air dry for one (1) minute. Do not rinse.
- moist surgical sites (such as inguinal fold): use one cloth to cleanse each 65 cm2 area (approximately 2 x 5 inches) of skin to be prepared. Vigorously scrub skin back and forth for 3 minutes, completely wetting treatment area, then discard. Allow area to air dry for one (1) minute. Do not rinse.
- discard each cloth after a single use
- after package has been opened discard any unused cloths

Directions

3M Skin and Nasal Antiseptic

- open package and remove bottle and swabs
- unscrew cap by turning cap counter-clockwise

Skin Application:

1. Apply to clean dry skin.
2. Dip one swab into solution and stir vigorously for 10 seconds. Withdraw the swab slowly to avoid wiping solution off during removal.
3. Scrub prep site for 2 minutes working from clean to dirty using both sides of the swab.
4. Repeat steps 2 & 3 using second swab.
5. Allow prep solution to dry. Do not blot.

Nasal Application:

1. Use a tissue to clean the inside of both nostrils including the inside tip of nostril. Discard.
2. Tilting the bottle slightly, dip one swab into solution and stir vigorously for 10 seconds. Withdraw the swab slowly to avoid wiping solution off during removal.
3. Insert swab comfortably into one nostril and rotate for 15 seconds covering all surfaces. Then focus on the inside tip of nostril and rotate for an additional 15 seconds. (swab 1)
4. Using a new swab: Repeat steps 2 & 3 with the other nostril. (swab 2)
5. Repeat the application in both nostrils using a fresh swab each time. (swabs 3 & 4)
6. Do not blow nose. If solution drips out of nose, it can be lightly dabbed with a tissue.

Inactive ingredients

2% Chlorhexidine Gluconate Cloth
aloe vera, dimethicone, fragrance, glucono-delta-lactone, glycerin, Igepal, polysorbate 20, propylene glycol, USP purified water
cloth: polyester

Inactive ingredients

3M Skin and Nasal Antiseptic
Lactic acid, lauramidopropylamine oxide, malic acid, polyquarternium-10, PPG-5-ceteth-10 phosphate, sodium hydroxide, sodium iodide, steareth-100, water, xylitol

PACKAGE LABEL

2% Chlorhexidine Gluconate* Cloth
NDC 053462–705–23

PACKAGE LABEL

3M Skin and Nasal Antiseptic
NDC 17518–060–04